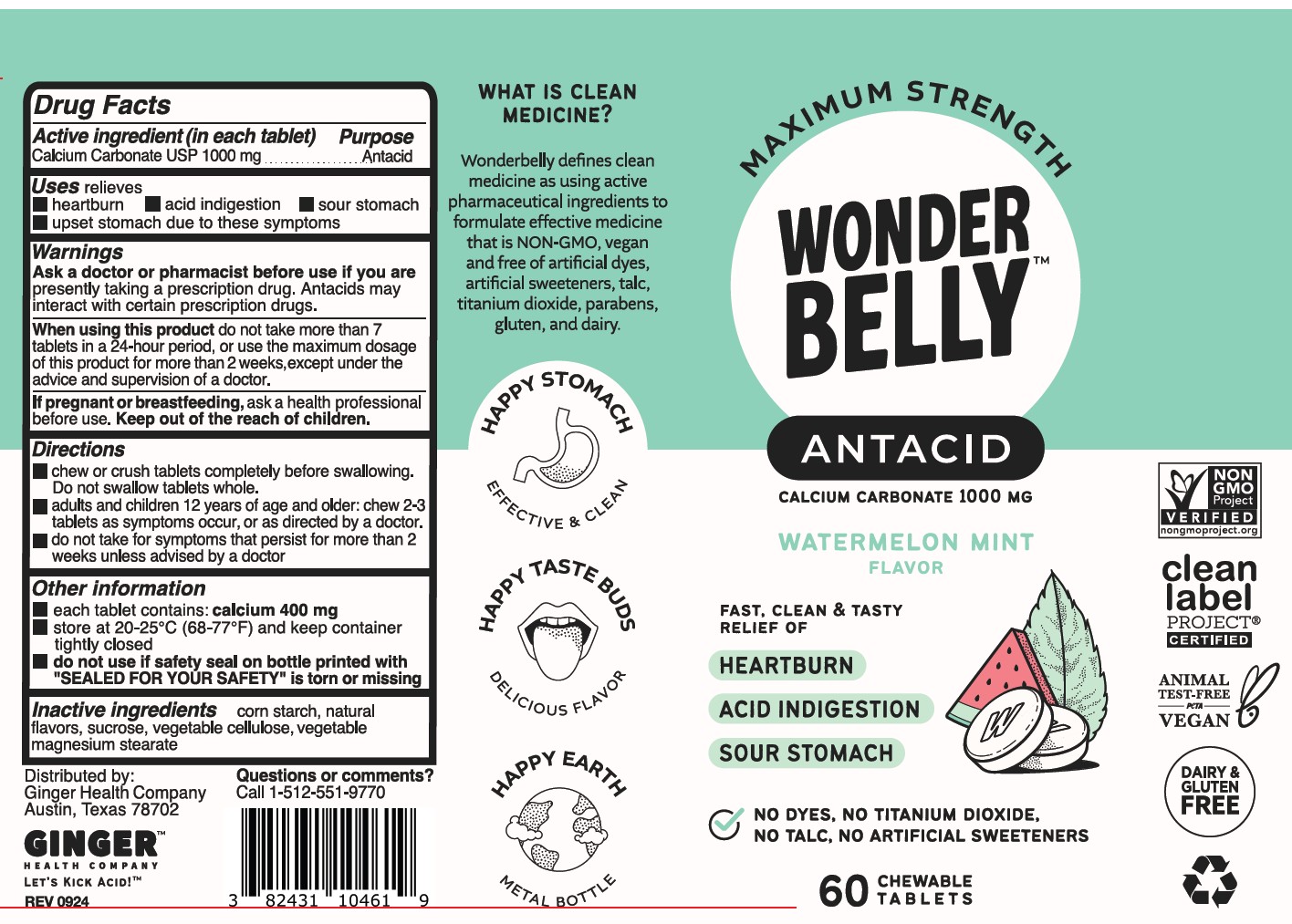 DRUG LABEL: Wonderbelly Maximum Strength Antacid
NDC: 82431-104 | Form: TABLET, CHEWABLE
Manufacturer: Ginger Health Company
Category: otc | Type: HUMAN OTC DRUG LABEL
Date: 20250915

ACTIVE INGREDIENTS: CALCIUM CARBONATE 1000 mg/1 1
INACTIVE INGREDIENTS: SUCROSE; MAGNESIUM STEARATE; MICROCRYSTALLINE CELLULOSE; STARCH, CORN

Wonderbelly Maximum Strength Antacid - calcium carbonate tablet, chewable

Active Ingredient (per tablet)

Calcium Carbonate USP 1000 mg

Purpose

Antacid

Uses

relieves

- heartburn
- acid indigestion
- sour stomach
- upset stomach associated with these symptoms

Warnings

Ask a doctor or pharmacist before use if you are presently taking a prescription drug. Antacids

may interact with certain prescription drugs.

When using this product

- do not take more than 7 tablets in 24 hours
- do not use the maximum dosage for more than 2 weeks, except under the advice and supervision of a doctor
- if pregnant or breast-feeding, ask a health professional before use

Keep out of reach of children.

Directions

- chew or crush tablets completely before swallowing. Do not swallow tablets whole.
- adults and children 12 years of age and over: chew 2-3 tablets as symptoms occur, or as directed by a doctor. Chew or crush tablets completely before swallowing.
- do not take for symptoms that persists for more than 2 weeks unless advised by a doctor

Other Information

- each tablet contains: calcium 400 mg
- store at room temperature and keep container tightly closed
- do not use if safety seal on bottle printed with "SEALED FOR YOUR SAFETY" is torn or missing

Inactive Ingredients

corn starch, natural flavors, sucrose, vegetable cellulose, vegetable magnesium stearate

Principal Display Panel

MAXIMUM STRENGTH

WONDERBELLY

ANTACID

calcium carbonate 1000 mg

Watermelon Mint Flavor

Fat, Clean, and Tasty Relief of

Heartburn

Acid Indigestion

Sour Stomach

No Dyes, No Titanium Dioxide, No Talc, No Artificial Sweeteners

60 Chewable Tablets